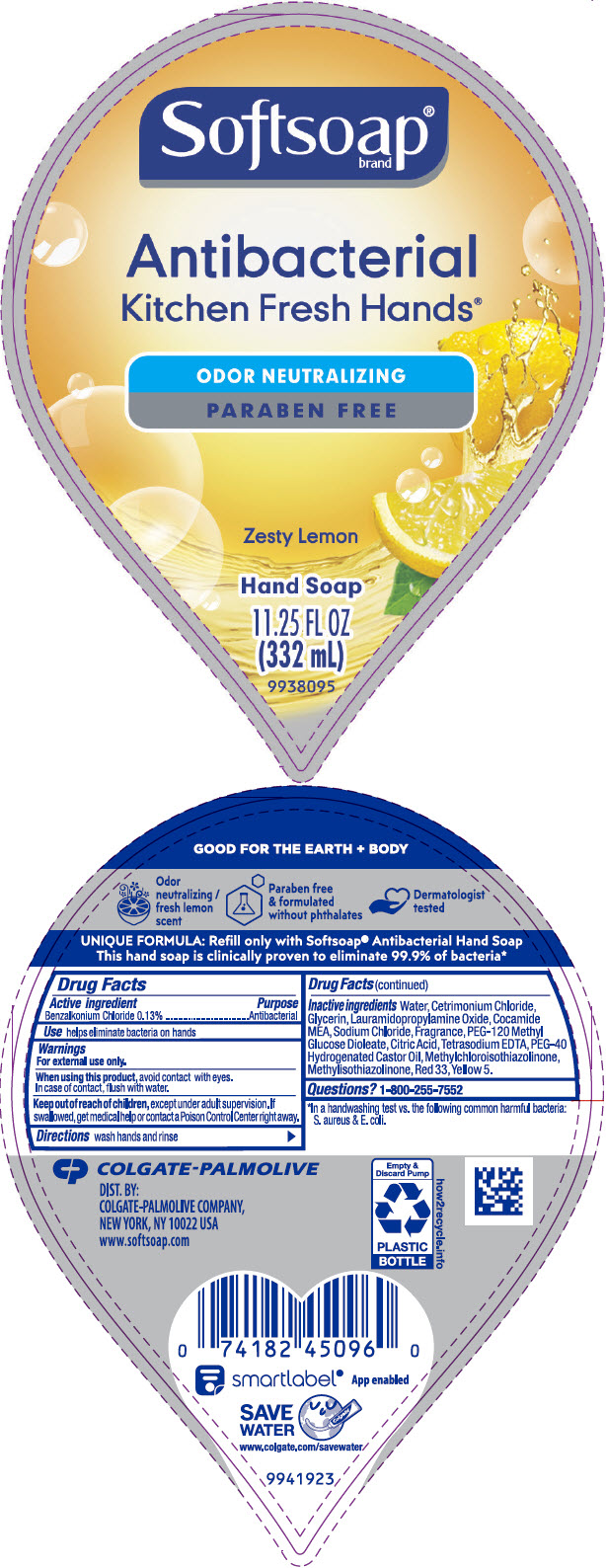 DRUG LABEL: Softsoap Antibacterial Kitchen Fresh Hands
NDC: 35000-098 | Form: LIQUID
Manufacturer: Colgate-Palmolive Company
Category: otc | Type: HUMAN OTC DRUG LABEL
Date: 20200901

ACTIVE INGREDIENTS: BENZALKONIUM CHLORIDE 1.33 mg/1 mL
INACTIVE INGREDIENTS: WATER; CETRIMONIUM CHLORIDE; GLYCERIN; LAURAMIDOPROPYLAMINE OXIDE; COCO MONOETHANOLAMIDE; SODIUM CHLORIDE; PEG-120 METHYL GLUCOSE DIOLEATE; CITRIC ACID MONOHYDRATE; EDETATE SODIUM; POLYOXYL 40 HYDROGENATED CASTOR OIL; METHYLCHLOROISOTHIAZOLINONE; METHYLISOTHIAZOLINONE; D&C RED NO. 33; FD&C YELLOW NO. 5

Softsoap® Antibacterial Kitchen Fresh Hands®

Drug Facts

Active ingredient

Benzalkonium Chloride 0.13%

Purpose

Antibacterial

Use

helps eliminate bacteria on hands

Warnings

For external use only

When using this product, avoid contact with eyes.

In case of contact, flush with water.

Keep out of reach of children, except under adult supervision. If swallowed, get medical help or contact a Poison Control Center right away.

Directions

wash hands and rinse

Inactive ingredients

Water, Cetrimonium Chloride, Glycerin, Lauramidopropylamine Oxide, Cocamide MEA, Sodium Chloride, Fragrance, PEG-120 Methyl Glucose Dioleate, Citric Acid, Tetrasodium EDTA, PEG-40 Hydrogenated Castor Oil, Methylchloroisothiazolinone, Methylisothiazolinone, Red 33, Yellow 5.

Questions?

1-800-255-7552

DIST. BY:
COLGATE-PALMOLIVE COMPANY,
NEW YORK, NY 10022 USA

PRINCIPAL DISPLAY PANEL - 332 mL Bottle Label

Softsoap®
brand

Antibacterial
Kitchen Fresh Hands®

ODOR NEUTRALIZING
PARABEN FREE

Zesty Lemon

Hand Soap
11.25 FL OZ
(332 mL)
9938095